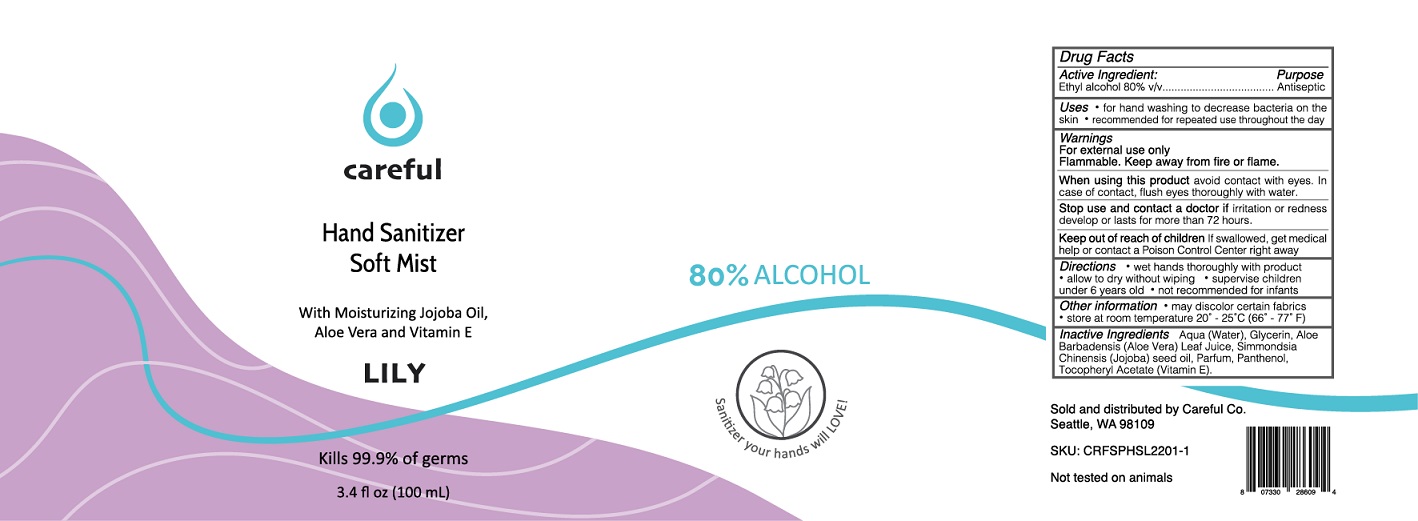 DRUG LABEL: careful Hand Sanitizer Lily
NDC: 80622-545 | Form: SPRAY
Manufacturer: Brainstem Innovations Co.
Category: otc | Type: HUMAN OTC DRUG LABEL
Date: 20220125

ACTIVE INGREDIENTS: ALCOHOL 80 mL/100 mL
INACTIVE INGREDIENTS: WATER; GLYCERIN; ALOE VERA LEAF; JOJOBA OIL; PANTHENOL; .ALPHA.-TOCOPHEROL ACETATE

careful Hand Sanitizer Soft Mist

Active Ingredient:

Ethyl alcohol 80% v/v

Purpose

Antiseptic

Uses

• for hand washing to decrease bacteria on the skin. • recommended for repeated use throughout the day

Warnings

For external use only

Flammable. Keep away from fire or flame.

When using this product avoid contact with eyes. In case of contact, flush eyes thoroughly with water.

Stop use and contact a doctor if irritation or redness develop or lasts for more than 72 hours.

Keep out of reach of children If swallowed, get medical help or contact a Poison Control Center right away

Directions

• wet hands thoroughly with product • allow to dry without wiping • supervise children under 6 years old • not recommended for infants

Other information

• may discolor certain fabrics • store at room temperature 20° - 25°C (66° - 77° F)

Inactive Ingredients

Aqua (Water), Glycerin, Aloe Barbadensis (Aloe Vera) Leaf Juice, Simmondsia Chinensis (Jojoba) seed oil, Parfum, Panthenol, Tocopheryl Acetate (Vitamin E).

With Moisturizing Jojoba Oil, Aloe Vera and Vitamin E

LILY

Kills 99.9% of germs

Sold and distributed by Careful Co.
Seattle, WA 98109

SKU: CRFSPHSL2201-1

Not tested on animals

Sanitizer your hands will LOVE!